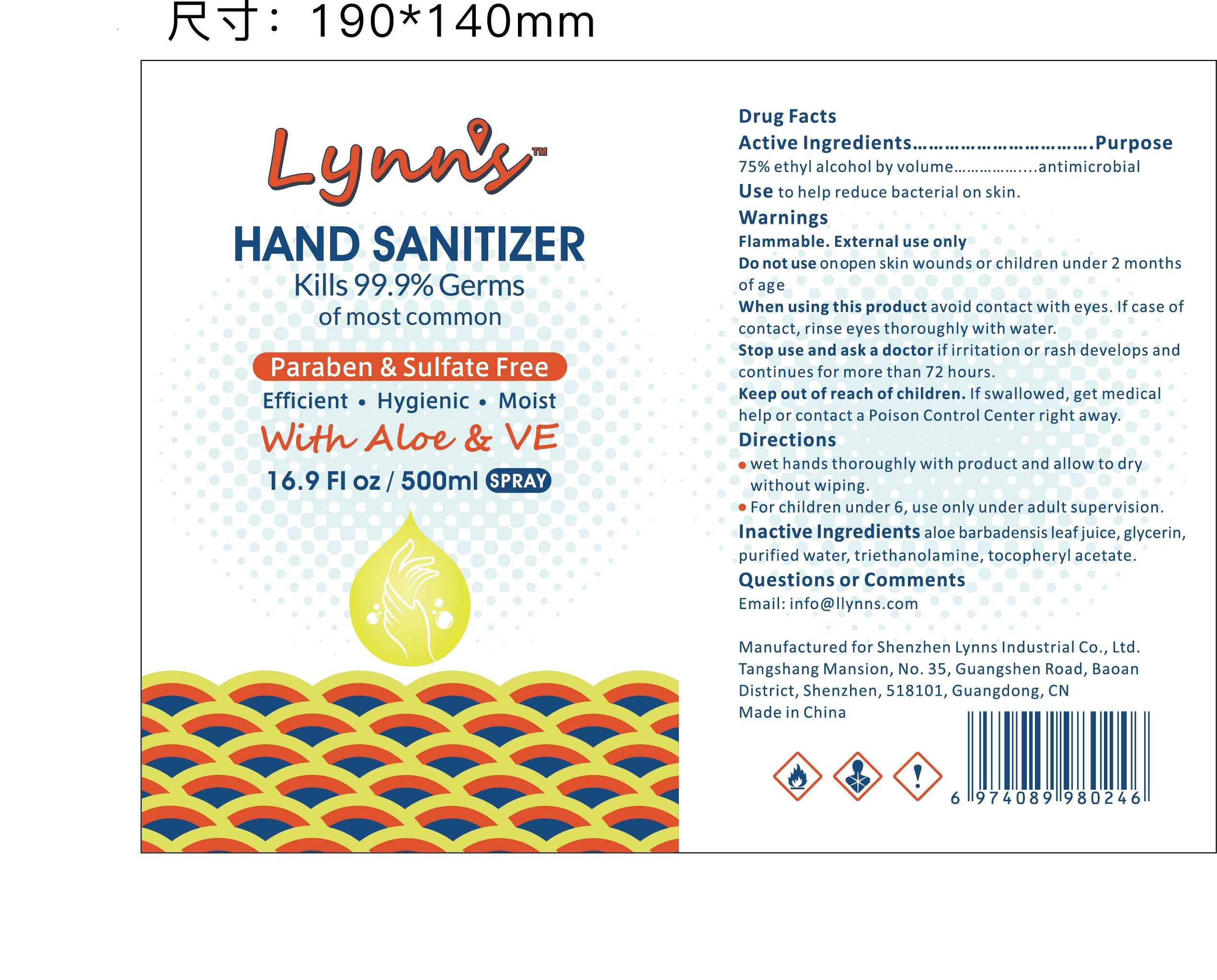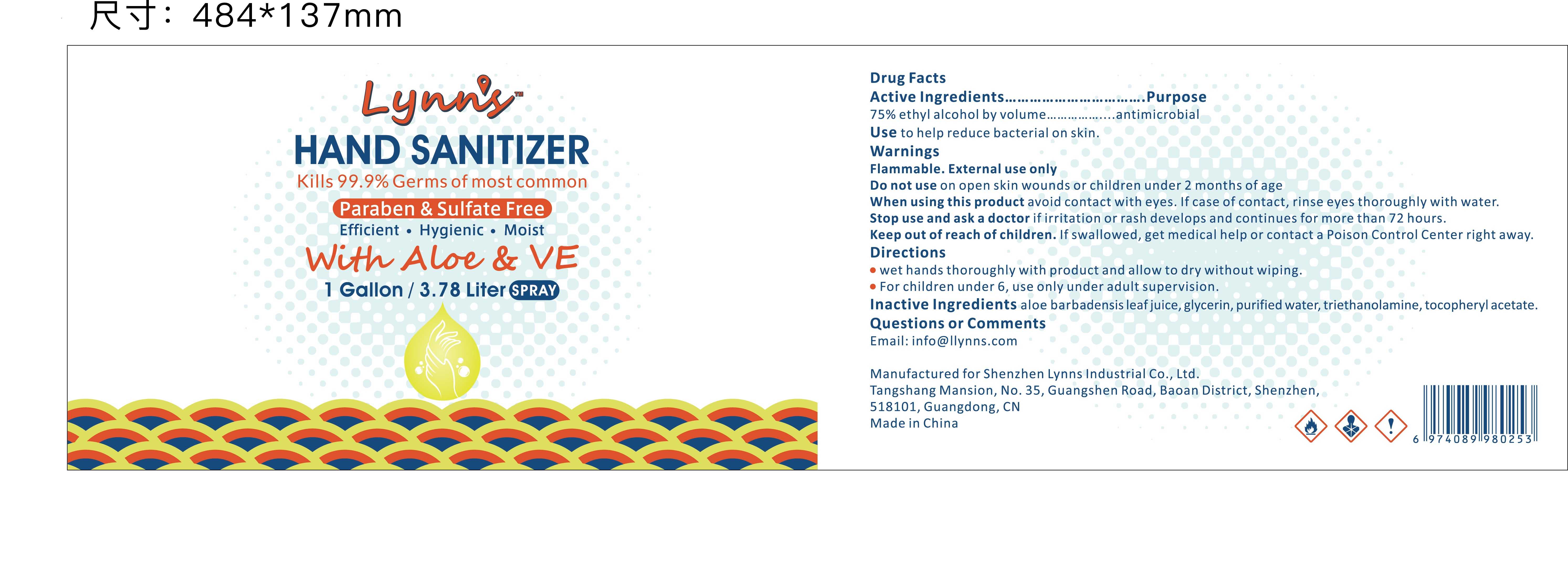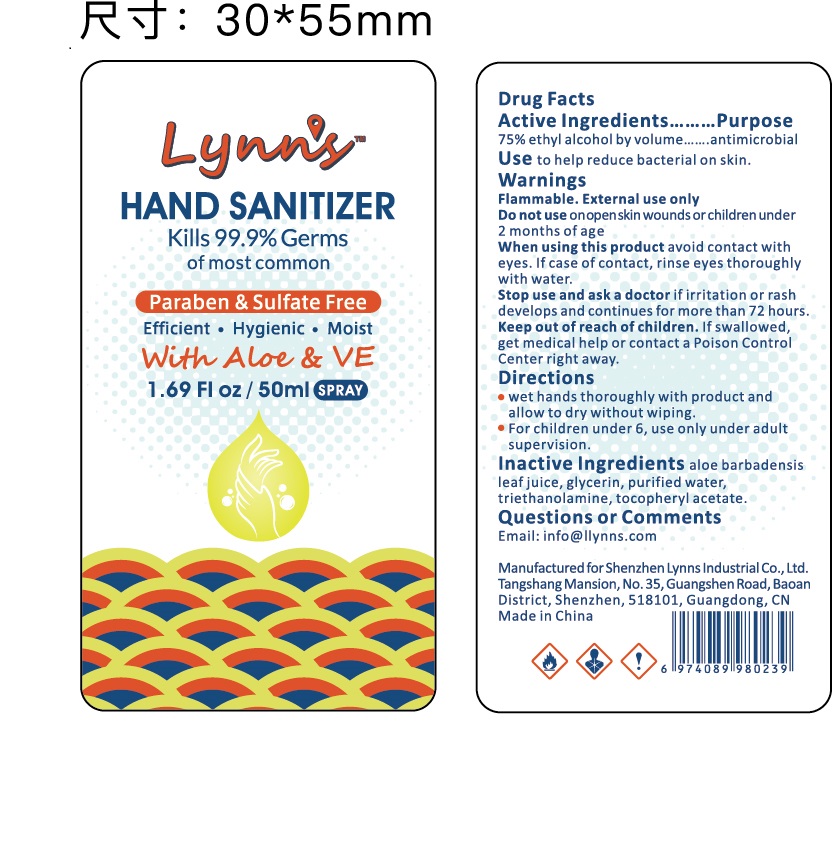 DRUG LABEL: Hand Sanitizer
NDC: 81422-009 | Form: SPRAY
Manufacturer: Shenzhen Lynns Industrial Co., Ltd.
Category: otc | Type: HUMAN OTC DRUG LABEL
Date: 20210118

ACTIVE INGREDIENTS: ALCOHOL 75 mL/100 mL
INACTIVE INGREDIENTS: GLYCERIN; ALOE VERA LEAF; WATER; TROLAMINE; ALPHA-TOCOPHEROL ACETATE

81422-009
Hand Sanitizer Spray

Active Ingredient(s)

75%ethyl alcohol by volume....antimicrobial

Purpose

antimicrobial

Use

Use to help reduce bacterial on skin.

Warnings

Flammable.External use only

Do not use on open skin wounds or children under 2 months of age

When using this product avoid contact with eyes.If case of contact, rinse eyes thoroughly with water.

Stop use and ask a doctor if irritation or rash develops and continues for more than 72 hours.

Keep out of reach of children.If swallowed, get medical help or contact a Poison Control Center right away.

Do not use on open skin wounds or children under 2 months of age

When using this product avoid contact with eyes.If case of contact, rinse eyes thoroughly with water.

Stop use and ask a doctor if irritation or rash develops and continues for more than 72 hours.

Keep out of reach of children.If swallowed, get medical help or contact a Poison Control Center right away.

Stop use and ask a doctor if irritation or rash develops and continues for more than 72 hours.

Keep out of reach of children.If swallowed, get medical help or contact a Poison Control Center right away.

Directions

·wet hands thoroughly with product and allow to dry without wiping.
·For children under 6, use only under adult supervision.

Other information

- Store between 15-30C (59-86F)
- Avoid freezing and excessive heat above 40C (104F)

Package Label - Principal Display Panel

81422-009-00--Hand Sanitizer Spray 500ml

81422-009-37--Hand Sanitizer Spray 1Gallon

81422-009-50--Hand Sanitizer Spray 50ml